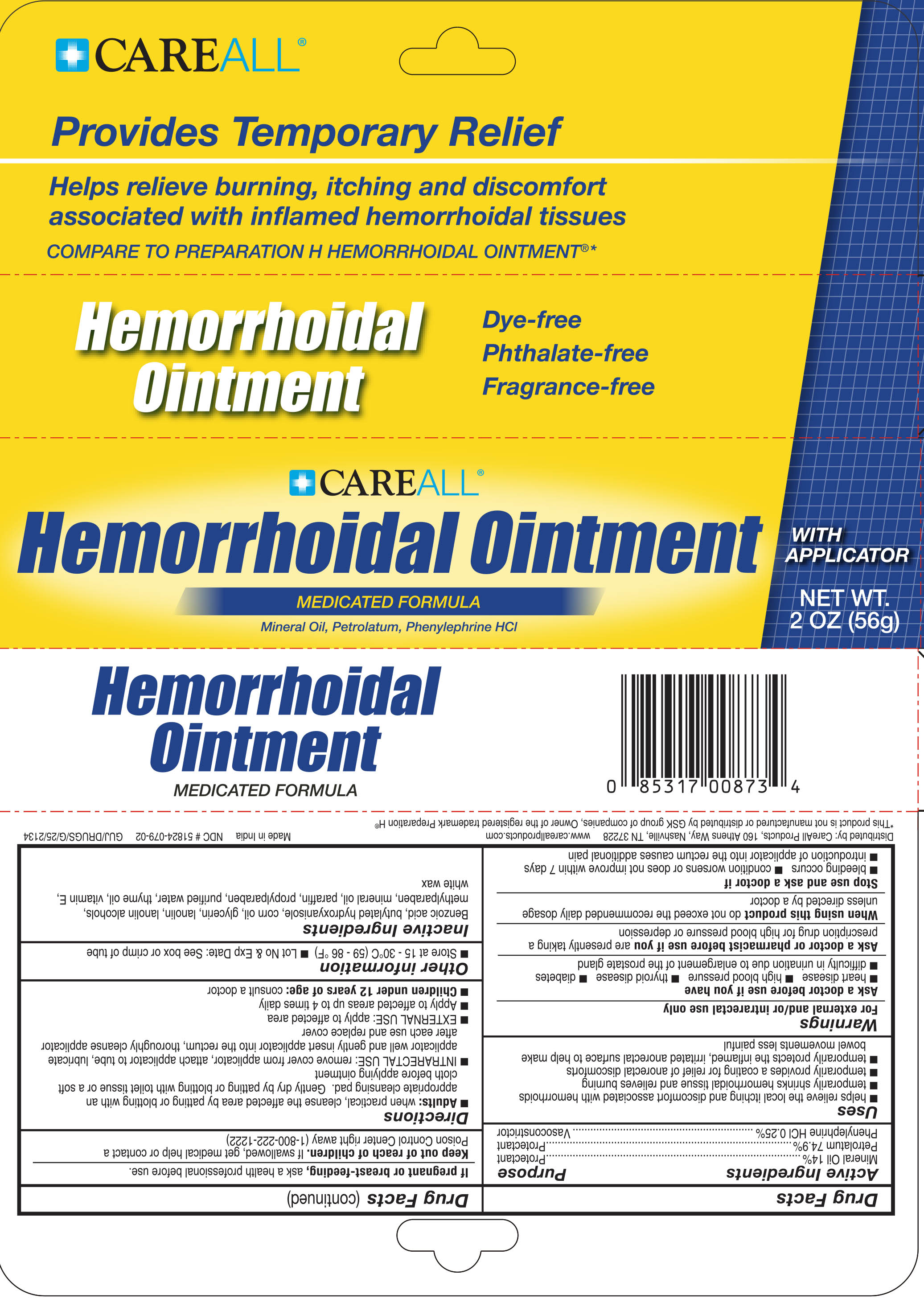 DRUG LABEL: CAREALL Hemorrhoidal
NDC: 51824-079 | Form: OINTMENT
Manufacturer: New World Imports, Inc
Category: otc | Type: HUMAN OTC DRUG LABEL
Date: 20251201

ACTIVE INGREDIENTS: MINERAL OIL 140 mg/1 g; PETROLATUM 749 mg/1 g; PHENYLEPHRINE HYDROCHLORIDE 2.5 mg/1 g
INACTIVE INGREDIENTS: BENZOIC ACID; BUTYLATED HYDROXYANISOLE; CORN OIL; GLYCERIN; LANOLIN; LANOLIN ALCOHOLS; METHYLPARABEN; PARAFFIN; PROPYLPARABEN; WATER; THYME OIL; .ALPHA.-TOCOPHEROL ACETATE; WHITE WAX

Active Ingredients

Mineral Oil 14%

Petrolatum 74.9%

Phenylephrine HCl 0.25%

Purpose

Active Ingredients Purposes
Mineral Oil 14%...................................................................Protectant
Petrolatum 74.9%................................................................Protectant
Phenylephrine HCl 0.25%...............................................Vasoconstrictor

Keep out of reach of children. If swallowed, get medical help or contact a Poison Control Center right away (1-800-222-1222)

Uses

 helps relieve the local itching and discomfort associated with hemorrhoids
 temporarily shrinks hemorrhoidal tissue and relieves burning
 temporarily provides a coating for relief of anorectal discomforts
 temporarily protects the inflamed, irritated anorectal surface to help make bowel movements less painful

Warnings

For external and/or intrarectal use only
Ask a doctor before use if you have
▪ heart disease ▪ high blood pressure ▪ thyroid disease ▪ diabetes
▪ difficulty in urination due to enlargement of the prostate gland
Ask a doctor or pharmacist before use if you arepresently taking a prescription drug for high blood pressure or depression
When using this product do not exceed the recommended daily dosage unless directed by a doctor
Stop use and ask a doctor if
▪ bleeding occurs ▪ condition worsens or does not improved within 7 days
▪ introduction of applicator into the rectum causes additional pain
If pregnant or breast-feeding, ask a health professional before use.

Directions

Adults:when practical, cleanse the affected area by patting or blotting with an appropriate cleansing pad. Gently dry by patting or blotting with toliet tissue or a soft cloth before applying ointment

- INTRARECTAL USE: remove cover from applicator, attach applicator to tube, lubricate applicator well and gently insert applicator into the rectum, thoroughly cleanse applicator after each use and replace cover
- EXTERNAL USE: apply to affected area
- Apply to affected areas up to 4 times daily

Children under 12 years of age: consult a doctor

Inactive Ingredients

Benzoic acid, butylated hydroxyanisole, corn oil, glycerin, lanolin, lanolin alcohols, methylparaben, mineral oil, paraffin, propylparaben, purified water, thyme oil, Vitamin E, white wax